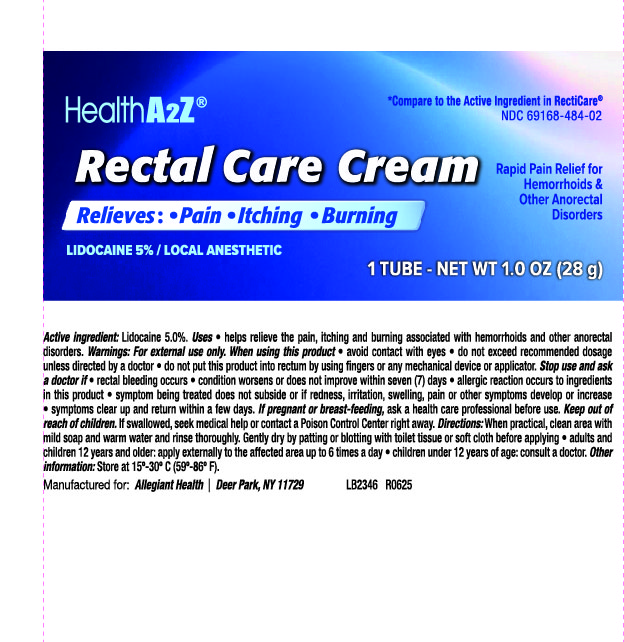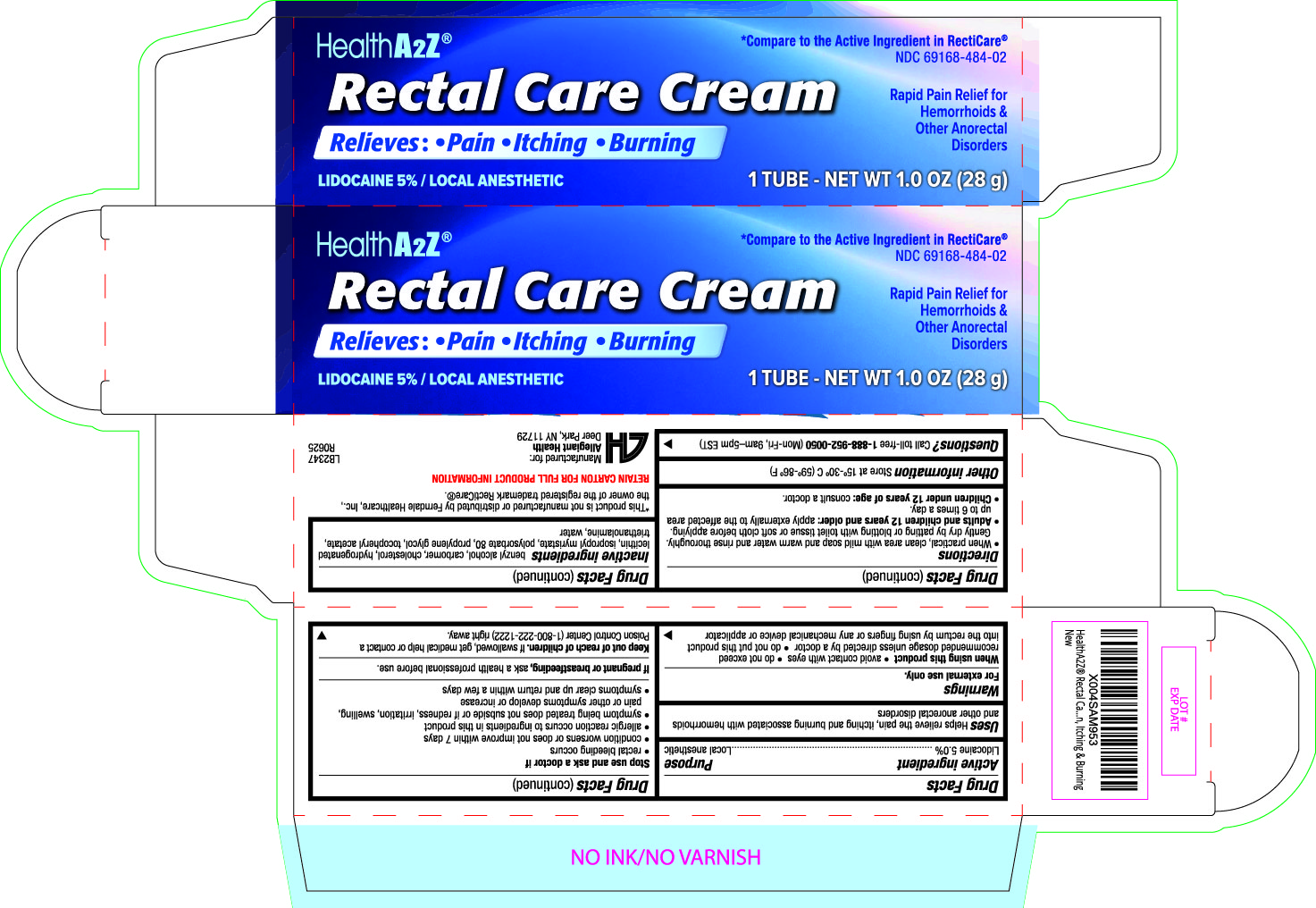 DRUG LABEL: Rectal Care Cream
NDC: 69168-484 | Form: CREAM
Manufacturer: Allegiant Health
Category: otc | Type: HUMAN OTC DRUG LABEL
Date: 20250707

ACTIVE INGREDIENTS: LIDOCAINE 5 g/100 g
INACTIVE INGREDIENTS: BENZYL ALCOHOL; CARBOMER; CHOLESTEROL; HYDROGENATED SOYBEAN LECITHIN; ISOPROPYL MYRISTATE; POLYSORBATE 80; PROPYLENE GLYCOL; TRIETHANOLAMINE; WATER

484 - Rectal Care Cream

Active ingredient(s)

Lidocaine 5.0%

Purpose

Local anesthetic

Use(s)

Helps relieve the pain, itching and burning associated with hemorrhoids
and other anorectal disorders

Warnings

For external use only.

When using this product

• avoid contact with eyes • do not exceed
recommended dosage unless directed by a doctor • do not put this product
into the rectum by using fingers or any mechanical device or applicator

Stop use and ask a doctor if

rectal bleeding occurs
• condition worsens or does not improve within 7 days
• allergic reaction occurs to ingredients in this product
• symptom being treated does not subside or if redness, irritation, swelling,
pain or other symptoms develop or increase
• symptoms clear up and return within a few days

If pregnant or breastfeeding,

ask a health professional before use.

Keep out of reach of children

In case of overdose, get medical help or contact a Poison Control Center right away.

Directions

• When practical, clean area with mild soap and warm water and rinse thoroughly.
Gently dry by patting or blotting with toilet tissue or soft cloth before applying.
• Adults and children 12 years and older: apply externally to the affected area up
to 6 times a day.
• Children under 12 years of age: consult a doctor.

Other information

Store at 15º-30º C (59º-86º F)

Inactive ingredients

benzyl alcohol, carbomer, cholesterol, hydrogenated
lecithin, isopropyl myristate, polysorbate 80, propylene glycol, tocopheryl acetate,
triethanolamine, water

Questions/Comments

Call 1-888-952-0050

(Monday-Friday 9 AM – 5 PM EST)

Principal Display Panel

Rectal Care Cream Label
Rectal Care Cream Carton